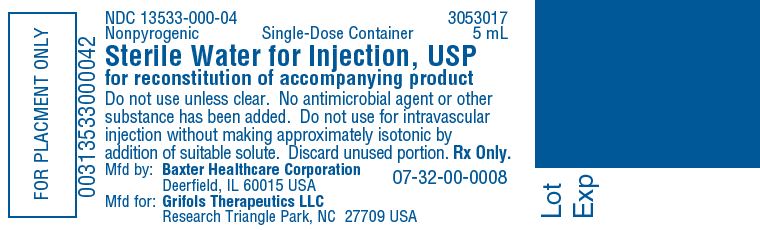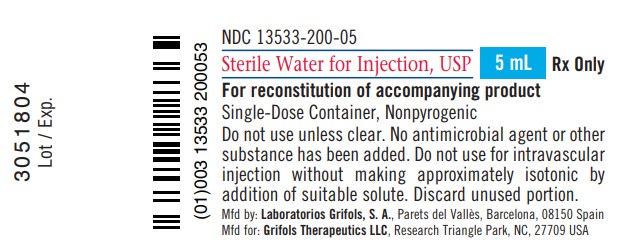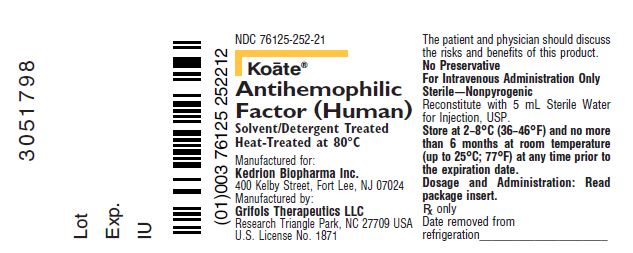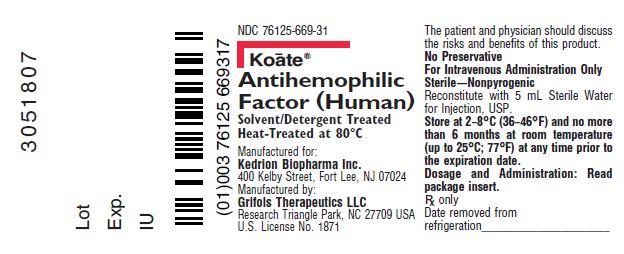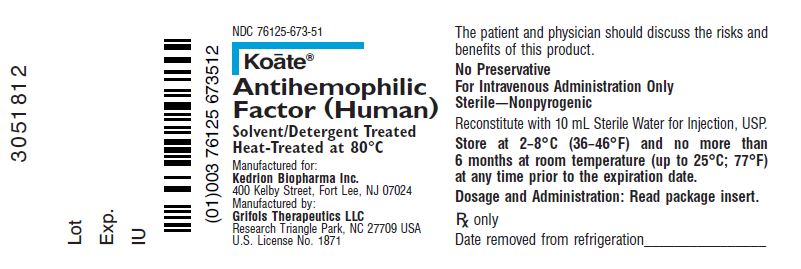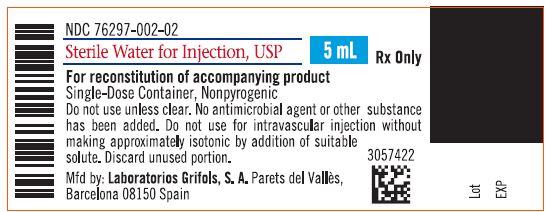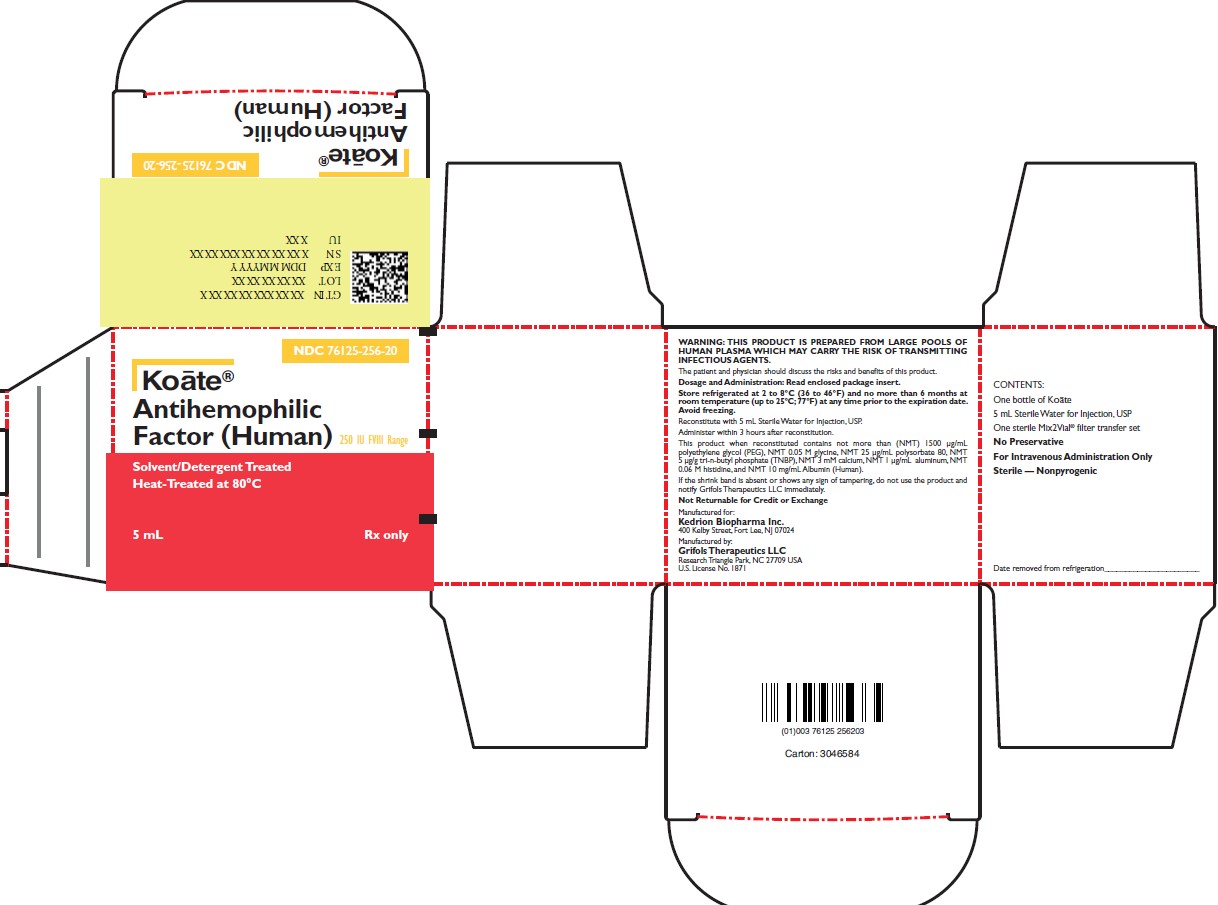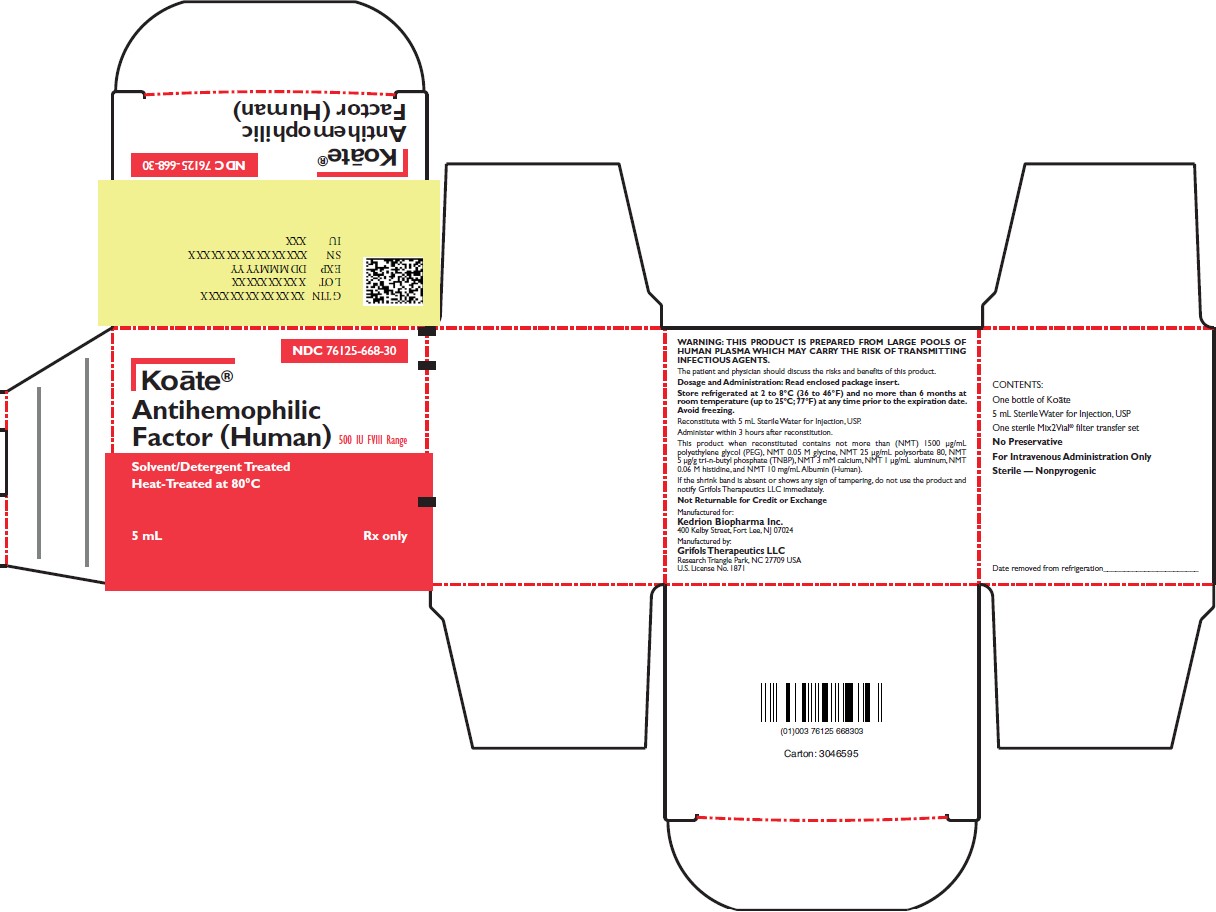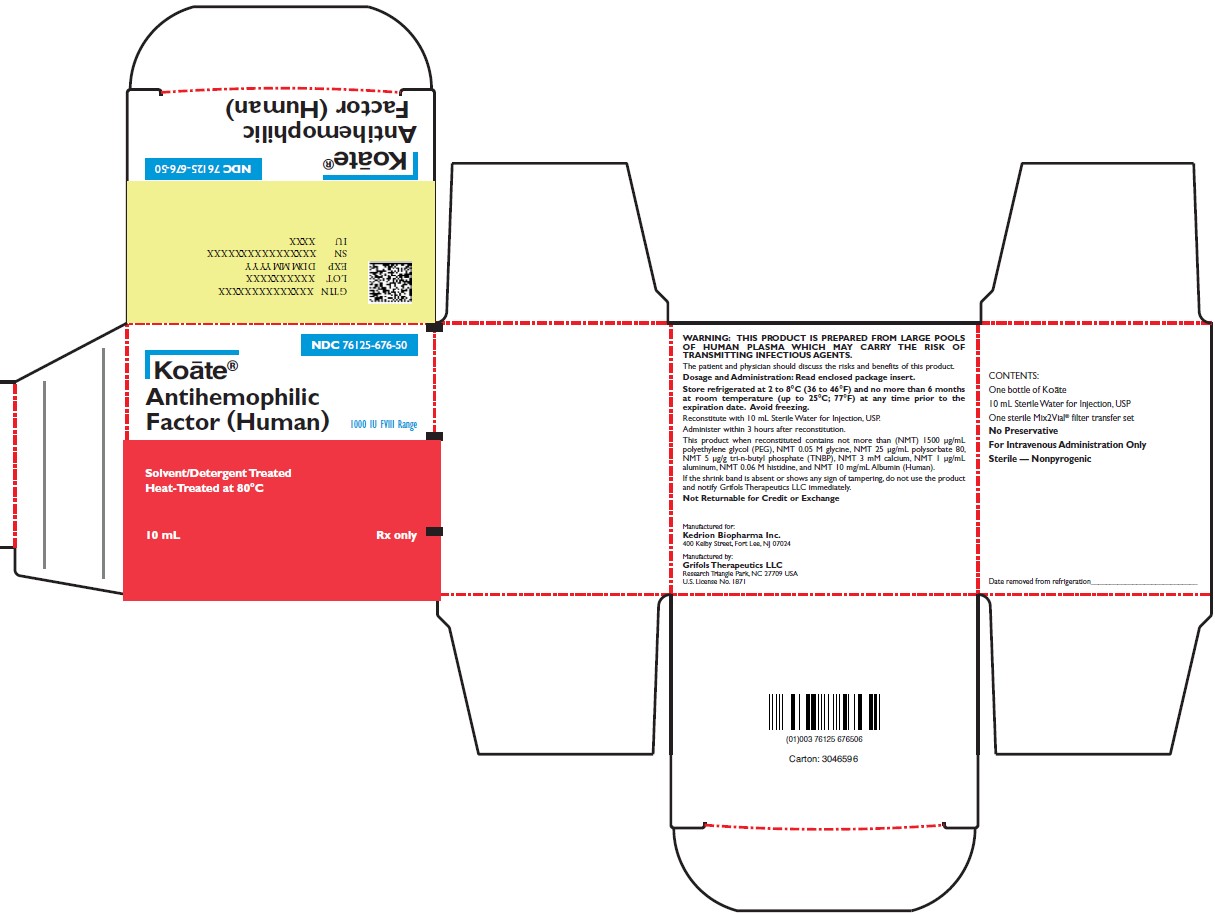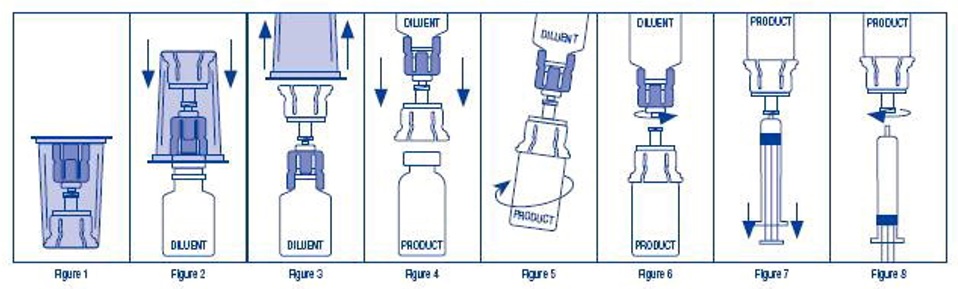 DRUG LABEL: Koate 
NDC: 76125-256 | Form: KIT | Route: INTRAVENOUS
Manufacturer: KEDRION BIOPHARMA, INC.
Category: other | Type: PLASMA DERIVATIVE
Date: 20231213

ACTIVE INGREDIENTS: Antihemophilic Factor Human 250 [iU]/5 mL
INACTIVE INGREDIENTS: Albumin Human; Sodium Chloride; Histidine; Calcium Chloride; Water

HIGHLIGHTS OF PRESCRIBING INFORMATION

These highlights do not include all the information needed to use KOĀTE® safely and effectively. See full prescribing information for KOĀTE.
KOĀTE®, Antihemophilic Factor (Human)
Lyophilized Powder for Solution for Intravenous Injection
Initial U.S. Approval: 1974

1 INDICATIONS AND USAGE

KOĀTE is a human plasma-derived antihemophilic factor indicated for the control and prevention of bleeding episodes or in order to perform emergency and elective surgery in patients with hemophilia A (hereditary Factor VIII deficiency). (1)

Limitation of Use
KOĀTE is not indicated for the treatment of von Willebrand disease.

2 DOSAGE AND ADMINISTRATION

For intravenous use after reconstitution only.

- Each vial of KOĀTE contains the labeled amount of Factor VIII in international units (IU). (2)
- Required Dose (IU) = Body Weight (kg) x Desired Factor VIII Rise (IU/dL or % of normal) x 0.5
- Frequency of KOĀTE administration is determined by the type of bleeding episode and the recommendation of the treating physician.

3 DOSAGE FORMS AND STRENGTHS

KOĀTE is available as a lyophilized powder for reconstitution in single-use vials of 250, 500, and 1,000 international units of Factor VIII activity. (3)

4 CONTRAINDICATIONS

Do not use in patients who have known hypersensitivity reactions, including anaphylaxis, to KOĀTE or its components. (4)

5 WARNINGS AND PRECAUTIONS

- Hypersensitivity reactions, including anaphylaxis, are possible. Should symptoms occur, discontinue KOĀTE and administer appropriate treatment. (5.1)
- Development of neutralizing antibodies (inhibitors) may occur. If expected plasma Factor VIII activity levels are not attained, or if bleeding is not controlled with an appropriate dose, perform an assay that measures Factor VIII inhibitor concentration. (5.2)
- Monitor for intravascular hemolysis and decreasing hematocrit values in patients with A, B or AB blood groups who are receiving large or frequent doses. (5.3)
- KOĀTE is made from human blood and therefore carries a risk of transmitting infectious agents, e.g., viruses, the variant Creutzfeldt-Jakob disease (vCJD) agent and, theoretically, the Creutzfeldt-Jakob disease (CJD) agent. (5.4)

6 ADVERSE REACTIONS

The most common adverse drug reactions (frequency ≥ 5% of subjects) observed in the clinical trial were nervousness, headache, abdominal pain, nausea, paresthesia and blurred vision. (6)

To report SUSPECTED ADVERSE REACTIONS, contact Grifols Therapeutics LLC at 1-800-520-2807 or FDA at 1-800-FDA-1088 or http://www.fda.gov/medwatch.

8 USE IN SPECIFIC POPULATIONS

Pediatric: clearance of Factor VIII (based on per kilogram body weight) is higher in children. Higher or more frequent dosing may be needed. (8.4)

FULL PRESCRIBING INFORMATION

1 INDICATIONS AND USAGE

KOĀTE® is a human plasma-derived antihemophilic factor indicated for the control and prevention of bleeding episodes or in order to perform emergency and elective surgery in patients with hemophilia A (hereditary Factor VIII deficiency).

Limitation of Use

KOĀTE is not indicated for the treatment of von Willebrand disease.

2 DOSAGE AND ADMINISTRATION

For intravenous use after reconstitution only.

2.1 Dose

- Dose and duration of treatment depend on the severity of the Factor VIII deficiency, location and extent of bleeding, and the patient’s clinical condition.
- Each vial of KOĀTE is labeled with the actual Factor VIII potency in international units (IU). Calculation of the required dose of Factor VIII is based on the empirical finding that one IU of Factor VIII per kg body weight raises the plasma Factor VIII activity by approximately 2% of normal activity or 2 IU/dL.
- The required dose can be determined using the following formula:
  Dose (IU) = Body Weight (kg) x Desired Factor VIII Rise (% normal or IU/dL) x 0.5
- Estimate the expected in vivo peak increase in Factor VIII level, expressed as IU/dL (or % normal), using the following formula:
  Estimated Increment of Factor VIII
  (% normal or IU/dL) = [Total Dose (IU)/Body Weight (kg)] x 2
- Patients may vary in their pharmacokinetic (e.g., half-life, in vivo recovery) and clinical responses. Base the dose and frequency on the individual clinical response.

Control and Prevention of Bleeding Episodes

A guide for dosing KOĀTE for the control and prevention of bleeding episodes (1,2) is provided in Table 1. Consideration should be given to maintaining a Factor VIII activity at or above the target range.

Table 1: Dosage Guidelines for Patients with Hemophilia A
Type of Bleeding | Factor VIII:C Level Required (% of normal) | Doses (IU/kg) | Frequency of Doses (hours) | Duration of Therapy (days)
Minor Large bruises Significant cuts or scrapes Uncomplicated joint hemorrhage | 30 | 15 | 12 (twice daily) | Until hemorrhage stops and healing has been achieved (1–2 days).
Moderate Nose, mouth and gum bleeds Dental extractions Hematuria | 50 | 25 | 12 (twice daily) | Until healing has been achieved (2–7 days, on average).
Major Joint hemorrhage Muscle hemorrhage Major trauma Hematuria Intracranial and intraperitoneal bleeding | 80-100 | Initial: 40-50 Maintenance: 25 | 12 (twice daily) | For at least 3–5 days Until healing has been achieved for up to 10 days. Intracranial hemorrhage may require prophylaxis therapy for up to 6 months.
Surgery | Prior to surgery: 80-100 After surgery: 60-100 | 40-50 30-50 | Once 12 (twice daily) | Prior to surgery For the next 7–10 days, or until healing has been achieved.

2.2 Preparation and Reconstitution

1. Use aseptic technique (clean and sanitized) and a flat work surface during the reconstitution procedure.
2. Bring the vials of KOĀTE and the diluent (Sterile Water for Injection) to room temperature before use.
3. Remove the shrink band from the KOĀTE vial. Do not use KOĀTE if the shrink band is absent or shows signs of tampering, and notify Grifols Therapeutics LLC immediately.
4. Remove the plastic cap from the KOĀTE vial and clean the top of the stopper with an alcohol swab. Allow the stopper to dry.
5. Repeat this step with the vial of sterile water.
6. Open the sterile Mix2Vial® package by peeling away the lid (Figure 1). Do not remove the device from the package.
7. Place the diluent vial upright on an even surface. Holding the diluent vial securely, push the blue end of the Mix2Vial straight down until the spike penetrates the stopper (Figure 2).
8. Remove the clear outer packaging from the Mix2Vial and discard it (Figure 3).
9. Place the KOĀTE vial upright on a flat surface, and invert the diluent vial with the Mix2Vial still attached.
10. While holding the KOĀTE vial securely on a flat surface, push the clear end of the Mix2Vial straight down until the spike penetrates the stopper (Figure 4). The diluent will automatically transfer into the KOĀTE vial by the vacuum contained within it.
  Note: If the Mix2Vial is connected at an angle, the vacuum may be released from the product vial and the diluent will not transfer into the product vial. If vacuum is lost, use a sterile syringe and needle to remove the sterile water from the diluent vial and inject it into the KOĀTE vial, directing the stream of fluid against the wall of the vial.
11. With the diluent and KOĀTE vials still attached to the Mix2Vial, agitate vigorously for 10 to 15 seconds, then gently swirl (Figure 5) until the powder is completely dissolved. Avoid excessive foaming. The reconstituted solution should be clear to opalescent. Do not use if particulate matter or discoloration is observed.
12. Remove the diluent vial and the blue end of the Mix2Vial (Figure 6) by holding each side of the vial adapter and twisting counterclockwise.
13. Draw air into an empty, sterile syringe. Connect the syringe to the clear end of the Mix2Vial by pressing and twisting clockwise, and push the air into the KOĀTE vial.
14. Immediately invert the system upside down and then draw the reconstituted KOĀTE into the syringe by pulling the plunger back slowly (Figure 7).
15. Detach the filled syringe from the Mix2Vial by turning counter-clockwise (Figure 8). Use KOĀTE within 3 hours after reconstitution. Do not refrigerate after reconstitution.

2.3 Administration

For intravenous administration only

- If the dose requires more than one vial of KOĀTE:
  - Reconstitute each vial using a new Mix2Vial.
  - Draw up all the solution into a single syringe.
- Visually inspect the final solution for particulate matter and discoloration prior to administration, whenever solution and container permit. Do not use if particulate matter or discoloration is observed.
- Attach the syringe to the connector end of an infusion set.
- Administer intravenously. The rate of administration should be determined by the patient’s comfort level, and no faster than 10 mL per minute.

3 DOSAGE FORMS AND STRENGTHS

KOĀTE is available as a lyophilized powder for reconstitution in single-use vials of 250, 500 and 1,000 IU of Factor VIII activity. The actual Factor VIII potency is labeled on each KOĀTE vial.

4 CONTRAINDICATIONS

KOĀTE is contraindicated in patients who have had hypersensitivity reactions, including anaphylaxis, to KOĀTE or its components. [see Description (11)]

5 WARNINGS AND PRECAUTIONS

5.1 Hypersensitivity Reactions

Hypersensitivity reactions, including anaphylaxis, are possible. Early signs of hypersensitivity reactions, which can progress to anaphylaxis, may include angioedema, chest tightness, hypotension, rash, nausea, vomiting, paresthesia, restlessness, wheezing and dyspnea. If hypersensitivity symptoms occur, discontinue use of the product immediately and administer appropriate emergency treatment.

5.2 Neutralizing Antibodies

The formation of neutralizing antibodies (inhibitors) to Factor VIII may occur. Monitor all patients for the development of Factor VIII inhibitors by appropriate clinical observations and laboratory tests. If expected plasma Factor VIII activity levels are not attained, or if bleeding is not controlled with an appropriate dose, perform an assay that measures Factor VIII inhibitor concentration. [see Warnings and Precautions (5.5)]

5.3 Intravascular Hemolysis

KOĀTE contains blood group isoagglutinins which are not clinically significant when small doses are used to treat minor bleeding episodes. However, when large and/or frequent doses of KOĀTE are given to patients with blood groups A, B, or AB, acute hemolytic anemia may occur, resulting in increased bleeding tendency or hyperfibrinogenemia. Monitor these patients for signs of intravascular hemolysis and falling hematocrit. [see Warnings and Precaustions (5.5)] Should this condition occur, leading to progressive hemolytic anemia, discontinue KOĀTE and consider administering serologically compatible Type O red blood cells and providing alternative therapy.

5.4 Transmissible Infectious Agents

Because KOĀTE is made from human blood, it may carry a risk of transmitting infectious agents, e.g., viruses, the variant Creutzfeldt-Jakob disease (vCJD) agent and, theoretically, the Creutzfeldt-Jakob disease (CJD) agent. There is also the possibility that unknown infectious agents may be present in the product. The risk that the product will transmit viruses has been reduced by screening plasma donors for prior exposure to certain viruses, by testing for the presence of certain current virus infections, and by inactivating and removing certain viruses during manufacture. Despite these measures, this product may still potentially transmit diseases.

Report all infections suspected by a physician possibly to have been transmitted by this product to Grifols Therapeutics LLC at 1-800-520-2807.

5.5 Monitoring: Laboratory Tests

- Monitor plasma Factor VIII activity levels by performing a validated test (e.g., one-stage clotting assay) to confirm that adequate Factor VIII levels have been achieved and maintained. [see Dosage and Administration (2.1)]
- Monitor for the development of Factor VIII inhibitors. Perform a Bethesda inhibitor assay if expected Factor VIII plasma levels are not attained, or if bleeding is not controlled with the expected dose of KOĀTE. Use Bethesda Units (BU) to report inhibitor levels.
- Monitor for intravascular hemolysis and decreasing hematocrit values in patients with A, B or AB blood groups who are receiving large or frequent doses of KOĀTE.

6 ADVERSE REACTIONS

The most common adverse drug reactions (frequency ≥ 5 % of subjects) observed in the clinical trial were nervousness, headache, abdominal pain, nausea, paresthesia and blurred vision.

6.1 Clinical Trials Experience

Because clinical studies are conducted under widely varying conditions, adverse reaction rates observed cannot be directly compared to rates in other clinical trials and may not reflect the rates observed in practice.

The safety assessment of KOĀTE is based on data from a 2-stage, safety, pharmacokinetic (PK) and efficacy clinical trial in which twenty subjects with severe hemophilia A (<1% endogenous Factor VIII activity) were evaluable for safety. Nineteen subjects were enrolled in Stage I of the trial, including 15 Caucasian, 3 Hispanic, and 1 Black subjects. The mean age was 29 years (range: 13.9 – 46.4 years). Nineteen subjects, including the 18 subjects who completed Stage I, and one new subject were enrolled in Stage II. The mean age was 30 years (range: 13.9 – 46.4). The subjects received a total of 1053 infusions. Ten adverse reactions related to 7 infusions were reported in 4 subjects. These were: nervousness (2 subjects [10%]), headache (1 subject [5%]), abdominal pain (1 subject [5%]), nausea (1 subject [5%]), paresthesia (1 subject [5%]), and blurred vision (1 subject [5%]).

Immunogenicity

Subjects were monitored for neutralizing antibodies (inhibitors) to Factor VIII by the Bethesda assay at baseline and at 8, 17 and 26 weeks. No evidence of inhibitor formation was observed in the clinical trial.

The detection of antibody formation is highly dependent on the sensitivity and specificity of the assay. Additionally, the observed incidence of antibody (including neutralizing antibody) positivity in an assay may be influenced by several factors including assay methodology, sample handling, timing of sample collection, concomitant medications, and underlying disease. For these reasons, it may be misleading to compare the incidence of antibodies to KOĀTE in the study described above with the incidence of antibodies in other studies or to other products.

6.2 Postmarketing Experience

Because postmarketing reporting of adverse reactions is voluntary and from a population of uncertain size, it is not always possible to reliably estimate the frequency of these reactions or establish a causal relationship to product exposure.

- Blood and Lymphatic System Disorders: Factor VIII inhibition, hemolytic anemia
- Immune System Disorders: Hypersensitivity including anaphylaxis, rash, pruritus
- Injury, Poisoning and Procedural Complications: Post-procedural hemorrhage
- Nervous System Disorders: Generalized clonic-tonic seizure

8 USE IN SPECIFIC POPULATIONS

8.1 Pregnancy

Risk Summary

There are no data with KOĀTE use in pregnant women to inform on drug-associated risk. Animal reproduction studies have not been conducted using KOĀTE. It is not known whether KOĀTE can cause fetal harm when administered to a pregnant woman or can affect reproduction capacity. KOĀTE should be given to a pregnant woman only if clearly needed. In the U.S. general population, the estimated background risk of major birth defects and miscarriage in clinically recognized pregnancies is 2-4% and 15-20%, respectively.

8.2 Lactation

Risk Summary

There is no information regarding the presence of KOĀTE in human milk, the effects on the breastfed infant, or the effects on milk production. The developmental and health benefits of breastfeeding should be considered along with the mother’s clinical need for KOĀTE and any potential adverse effects on the breast-fed infant from KOĀTE or from the underlying maternal condition.

8.4 Pediatric Use

Safety and efficacy studies have been performed in 20 previously treated pediatric patients aged 2.5 to 16 years. Subjects received 208 infusions of KOĀTE for treatment or control of bleeding episodes, including perioperative management, and routine prophylaxis. Children have shorter half-life and lower recovery of Factor VIII than adults. Because clearance of Factor VIII (based on per kilogram body weight) is higher in children, higher or more frequent dosing may be needed.

8.5 Geriatric Use

Clinical studies of KOĀTE did not include any subjects aged 65 and over to determine whether they respond differently from younger subjects. Individualize dose selection for geriatric patients.

11 DESCRIPTION

KOĀTE, Antihemophilic Factor (Human), is a sterile, stable, dried concentrate of human antihemophilic factor in lyophilized powder form for reconstitution for intravenous injection. The product is supplied in single-use vials containing nominally 250, 500, or 1,000 international units (IU or units). Each vial of KOĀTE is labeled with the actual amount of Factor VIII expressed in IU. One IU is defined by the current World Health Organization International Standard for Factor VIII concentrate, which can be traced to the level of Factor VIII found in 1 mL of fresh pooled human plasma. The final product when reconstituted as directed contains not more than (NMT) 1500 μg/mL polyethylene glycol (PEG), NMT 0.05 M glycine, NMT 25 μg/mL polysorbate 80, NMT 5 μg/g tri-n-butyl phosphate (TNBP), NMT 3 mM calcium, NMT 1 μg/mL aluminum, NMT 0.06 M histidine, and NMT 10 mg/mL human albumin.

KOĀTE is purified from the cold insoluble fraction of pooled human plasma; the manufacturing process includes solvent/detergent (TNBP and polysorbate 80) treatment and heat treatment of the lyophilized final container. A gel permeation chromatography step serves the dual purpose of reducing the amount of TNBP and polysorbate 80 as well as increasing the purity of the Factor VIII in KOĀTE to 300 to 1,000 times over whole plasma. When reconstituted as directed, KOĀTE contains approximately 50 to 150 times as much Factor VIII as an equal volume of fresh plasma. The specific activity after addition of human albumin is in the range of 9 to 22 units/mg protein. KOĀTE also contains naturally occurring von Willebrand factor, which is co-purified as part of the manufacturing process.

The KOĀTE manufacturing process includes two dedicated steps with virus inactivation capacity. The solvent/detergent treatment step has the capacity to inactivate enveloped viruses (such as HIV, HCV, HBV, and WNV). Heat treatment at 80ºC for 72 hours has the capacity to inactivate enveloped viruses (such as HIV and HCV) as well as non‑enveloped viruses (such as HAV and B19V). The polyethylene glycol (PEG) precipitation/depth filtration step has the capacity to remove both enveloped and non‑enveloped viruses. The accumulated virus reduction factors for KOĀTE manufacturing process are presented in Table 2.

Table 2: Virus Clearance Capacity (Log10) for the Antihemophilic Factor (Human) Manufacturing Process
 | Enveloped Viruses |  |  |  |  | Non-enveloped Viruses
 | HIV-1 | BVDV | PRV | VSV | WNV | Reo3 | HAV | PPV
Model for | HIV-1/2 | HCV | Large enveloped DNA viruses (e.g., herpes virus) | Enveloped RNA viruses | WNV | Non-enveloped viruses | HAV | B19V
Global Reduction Factor | ≥ 12.0 | ≥ 11.5 | ≥ 10.8 | ≥ 10.9 | ≥ 5.9* | ≥ 9.9 | ≥ 5.5 | 4.8
* WNV inactivation was evaluated only for the solvent/detergent treatment step

Additionally, the KOĀTE manufacturing process was investigated for its capacity to decrease the infectivity of an experimental agent of transmissible spongiform encephalopathy (TSE), considered a model for the variant Creutzfeldt-Jakob disease (vCJD) and Creutzfeldt-Jakob disease (CJD) agents. The manufacturing process has been shown to decrease TSE infectivity of that experimental model agent (a total of 5.1 log10 reduction), providing reasonable assurance that low levels of vCJD/CJD agent infectivity, if present in the starting material, would be removed.

12 CLINICAL PHARMACOLOGY

12.1 Mechanism of Action

KOĀTE temporarily replaces the missing clotting Factor VIII that is needed for effective hemostasis.

12.2 Pharmacodynamics

Hemophilia A is a bleeding disorder characterized by a deficiency of functional coagulation Factor VIII, resulting in a prolonged plasma clotting time as measured by the activated partial thromboplastin time (aPTT) assay. Treatment with KOĀTE normalizes the aPTT over the effective dosing period.

12.3 Pharmacokinetics

The pharmacokinetics (PK) of KOĀTE were evaluated in a prospective, two-stage clinical trial of 20 previously treated patients (PTPs) with severe hemophilia A. In Stage I, the PK parameters for 19 subjects were based on plasma Factor VIII activity after a single intravenous infusion of 50 IU/kg of KOĀTE. Bioequivalence of the dry heat-treated KOĀTE to the unheated KOĀTE was demonstrated by comparison of Cmaxand the area under the curve, AUC0-48 (Table 3). The incremental in vivo recovery ten minutes after infusion of dry heat-treated KOĀTE was 1.90% unit/kg (unheated KOĀTE was 1.82% units/kg). Mean biologic half-life was 16.1 hours.

In Stage II of the study, participants received KOĀTE treatments for six months on home therapy with a median of 52 days (range 23 to 94 days). At the end of 6 months, the mean AUC0-48 was 1471 ± 237 unit*hour/100 mL, the Cmax was 99 ± 13 unit/100 mL, and the t1/2was 16 ± 3.9 hours.

Table 3: PK Parameters of KOĀTE (Stage I of Crossover Trial)
Parameter | KOĀTE Dry Heat-treated (mean ± SD) | KOĀTE Unheated (mean ± SD)
AUC0-48 (IU hr/mL) | 1432 ±288 | 1477 ± 343
Cmax (IU/mL) | 103 ± 19 | 99 ± 20
Tmax (hr) | 0.41 ± 0.26 | 0.43 ± 0.44
Half life (hr) | 16.1 ± 3.2 | 16.1 ± 5.1

14 CLINICAL STUDIES

The efficacy of KOĀTE for the treatment of bleeding episodes was demonstrated in a 2-stage, safety, PK and efficacy clinical trial. Stage I was a randomized, single-blind, single-dose, crossover, and PK study comparing heat-treated KOĀTE with unheated KOĀTE. Nineteen subjects were randomized and received a single dose of 50 IU/kg of either heated KOĀTE or unheated KOĀTE for PK assessment. Stage II was a 6 month open-label safety study conducted at two hemophilia centers. Nineteen subjects received KOĀTE, including for on-demand treatment and control of bleeding episodes. The study populations included 15 Caucasians, 3 Hispanic, and 1 Black subjects. A total of 306 bleeding episodes were treated, of which 82% were treated with a single infusion of Factor VIII.

15 REFERENCES

1. Srivastava A, Brewer AK, Mauser-Bunschoten EP, et al. Guidelines for the management of hemophilia. Haemophilia 2013;19(1):e1-47.
2. Abildgaard CF. Current concepts in the management of hemophilia. Semin Hematol 1975;12(3):223-32.

16 HOW SUPPLIED/STORAGE AND HANDLING

How Supplied

KOĀTE is supplied in single-use vials containing 250, 500 or 1,000 IU of Factor VIII activity, packaged with 5 mL or 10 mL of Sterile Water for Injection, and a Mix2Vial® transfer device. The actual amount of KOĀTE in IU is stated on each carton and vial label.

Components used in the packaging of KOĀTE are not made with natural rubber latex.

Strength | Carton (Kit) NDC Number
250 IU | 76125-256-20, 76125-257-25 or 76125-259-02
500 IU | 76125-668-30, 76125-663-50 or 76125-665-02
1,000 IU | 76125-676-50, 76125-678-10 or 76125-679-12

Storage and Handling

- Store KOĀTE in its original package to protect it from light.
- Store the KOĀTE package at 2 to 8°C (36 to 46°F). Do not freeze.
- KOĀTE may also be stored at room temperature (up to 25°C or 77°F) for up to 6 months.
- Do not use after the expiration date.
- Use reconstituted KOĀTE immediately or within 3 hours of reconstitution.

17 PATIENT COUNSELING INFORMATION

- Inform patients to immediately report the following early signs and symptoms of hypersensitivity reactions to their healthcare professional: angioedema, chest tightness, hypotension, rash, nausea, vomiting, paresthesia, restlessness, wheezing and dyspnea. [see Warnings and Precautions (5.1)]
- Inform patients that the development of inhibitors to Factor VIII is a possible complication of treatment with KOĀTE. Advise the patients to contact their healthcare provider for further treatment and/or assessment if they experience a lack of clinical response to KOĀTE because this may be a manifestation of an inhibitor. [see Warnings and Precautions (5.2)]
- Inform patients that KOĀTE is made from human plasma and may carry a risk of transmitting infectious agents. While the risk that KOĀTE can transmit an infection has been reduced by screening plasma donors for prior exposure, testing donated plasma, and inactivating or removing certain viruses during manufacturing, patients should report any symptoms that concern them. [see Warnings and Precautions (5.4)]

Manufactured for:
Kedrion Biopharma Inc.
400 Kelby Street, Fort Lee, NJ 07024
Manufactured by:
Grifols Therapeutics LLC
Research Triangle Park, NC 27709 USA
U.S. License No. 1871
Mix2Vial® is a registered trademark of Medimop Medical Projects Ltd.
3058092

PACKAGE LABEL

NDC 76125-256-20
Koāte®
Antihemophilic Factor (Human)
250 IU FVIII Range
Solvent/Detergent Treated
Heat-Treated at 80°C
5 mL
Rx only
WARNING: THIS PRODUCT IS PREPARED FROM LARGE POOLS OF HUMAN PLASMA WHICH MAY CARRY THE RISK OF TRANSMITTING INFECTIOUS AGENTS.
The patient and physician should discuss the risks and benefits of this product.
Dosage and Administration: Read enclosed package insert.
Store refrigerated at 2 to 8°C (36 to 46°F) and no more than 6 months at room temperature (up to 25°C; 77°F) at any time prior to the expiration date.
Avoid freezing.
Reconstitute with 5 mL Sterile Water for Injection, USP.
Administer within 3 hours after reconstitution.
This product when reconstituted contains not more than (NMT) 1500 μg/mL polyethylene glycol (PEG), NMT 0.05 M glycine, NMT 25 μg/mL polysorbate 80, NMT 5 μg/g tri-n-butyl phosphate (TNBP), NMT 3 mM calcium, NMT 1 μg/mL aluminum, NMT 0.06 M histidine, and NMT 10 mg/mL Albumin (Human).
If the shrink band is absent or shows any sign of tampering, do not use the product and notify Grifols Therapeutics LLC immediately.
Not Returnable for Credit or Exchange
Manufactured for:
Kedrion Biopharma Inc.
400 Kelby Street, Fort Lee, NJ 07024
Manufactured by:
Grifols Therapeutics LLC
Research Triangle Park, NC 27709 USA
U.S. License No. 1871
CONTENTS:
One bottle of Koāte
5 mL Sterile Water for Injection, USP
One sterile Mix2Vial® filter transfer set
No Preservative
For Intravenous Administration Only
Sterile — Nonpyrogenic
Date removed from refrigeration_______________________
GTIN XXXXXXXXXXXXXX
LOT XXXXXXXXXX
EXP DDMMMYYYY
SN XXXXXXXXXXXXXXXX
IU XXX
NDC 76125-256-20
Koāte®
Antihemophilic Factor (Human)
Carton: 3046584

NDC 76125-252-21
Koāte®
Antihemophilic Factor (Human)
Solvent/Detergent Treated
Heat-Treated at 80°C
Manufactured for:
Kedrion Biopharma Inc.
400 Kelby Street, Fort Lee, NJ 07024
Manufactured by:
Grifols Therapeutics LLC
Research Triangle Park, NC 27709 USA
U.S. License No. 1871
The patient and physician should discuss the risks and benefits of this product.
No Preservative
For Intravenous Administration Only
Sterile—Nonpyrogenic
Reconstitute with 5 mL Sterile Water for Injection, USP.
Store at 2–8°C (36–46°F) and no more than 6 months at room temperature (up to 25°C; 77°F) at any time prior to the expiration date.
Dosage and Administration: Read package insert.
Rx only
Date removed from refrigeration_____________________
Lot
Exp.
IU
3051798

NDC 76125-668-30
Koāte®
Antihemophilic
Factor (Human)
500 IU FVIII Range
Solvent/Detergent Treated
Heat-Treated at 80°C
5 mL
Rx only
WARNING: THIS PRODUCT IS PREPARED FROM LARGE POOLS OF HUMAN PLASMA WHICH MAY CARRY THE RISK OF TRANSMITTING INFECTIOUS AGENTS.
The patient and physician should discuss the risks and benefits of this product.
Dosage and Administration: Read enclosed package insert.
Store refrigerated at 2 to 8°C (36 to 46°F) and no more than 6 months at room temperature (up to 25°C; 77°F) at any time prior to the expiration date.
Avoid freezing.
Reconstitute with 5 mL Sterile Water for Injection, USP.
Administer within 3 hours after reconstitution.
This product when reconstituted contains not more than (NMT) 1500 μg/mL polyethylene glycol (PEG), NMT 0.05 M glycine, NMT 25 μg/mL polysorbate 80, NMT 5 μg/g tri-n-butyl phosphate (TNBP), NMT 3 mM calcium, NMT 1 μg/mL aluminum, NMT 0.06 M histidine, and NMT 10 mg/mL Albumin (Human).
If the shrink band is absent or shows any sign of tampering, do not use the product and notify Grifols Therapeutics LLC immediately.
Not Returnable for Credit or Exchange
Manufactured for:
Kedrion Biopharma Inc.
400 Kelby Street, Fort Lee, NJ 07024
Manufactured by:
Grifols Therapeutics LLC
Research Triangle Park, NC 27709 USA
U.S. License No. 1871
CONTENTS:
One bottle of Koāte
5 mL Sterile Water for Injection, USP
One sterile Mix2Vial® filter transfer set
No Preservative
For Intravenous Administration Only
Sterile — Nonpyrogenic
Date removed from refrigeration_______________________
GTIN XXXXXXXXXXXXXX
LOT XXXXXXXXXX
EXP DDMMMYYYY
SN XXXXXXXXXXXXXXXX
IU XXX
NDC 76125-668-30
Koāte®
Antihemophilic
Factor (Human)
Carton: 3046595

NDC 76125-669-31
Koāte®
Antihemophilic Factor (Human)
Solvent/Detergent Treated
Heat-Treated at 80°C
Manufactured for:
Kedrion Biopharma Inc.
400 Kelby Street, Fort Lee, NJ 07024
Manufactured by:
Grifols Therapeutics LLC
Research Triangle Park, NC 27709 USA
U.S. License No. 1871
The patient and physician should discuss the risks and benefits of this product.
No Preservative
For Intravenous Administration Only
Sterile—Nonpyrogenic
Reconstitute with 5 mL Sterile Water for Injection, USP.
Store at 2–8°C (36–46°F) and no more than 6 months at room temperature (up to 25°C; 77°F) at any time prior to the expiration date.
Dosage and Administration: Read package insert.
Rx only
Date removed from refrigeration_____________________
Lot
Exp.
IU
3051807

NDC 76125-676-50
Koāte®
Antihemophilic
Factor (Human)
1000 IU FVIII Range
Solvent/Detergent Treated
Heat-Treated at 80°C
10 mL
Rx only
WARNING: THIS PRODUCT IS PREPARED FROM LARGE POOLS OF HUMAN PLASMA WHICH MAY CARRY THE RISK OF TRANSMITTING INFECTIOUS AGENTS.
The patient and physician should discuss the risks and benefits of this product.
Dosage and Administration: Read enclosed package insert.
Store refrigerated at 2 to 8°C (36 to 46°F) and no more than 6 months at room temperature (up to 25°C; 77°F) at any time prior to the expiration date.
Avoid freezing.
Reconstitute with 10 mL Sterile Water for Injection, USP.
Administer within 3 hours after reconstitution.
This product when reconstituted contains not more than (NMT) 1500 μg/mL polyethylene glycol (PEG), NMT 0.05 M glycine, NMT 25 μg/mL polysorbate 80, NMT 5 μg/g tri-n-butyl phosphate (TNBP), NMT 3 mM calcium, NMT 1 μg/mL aluminum, NMT 0.06 M histidine, and NMT 10 mg/mL Albumin (Human).
If the shrink band is absent or shows any sign of tampering, do not use the product and notify Grifols Therapeutics LLC immediately.
Not Returnable for Credit or Exchange
Manufactured for:
Kedrion Biopharma Inc.
400 Kelby Street, Fort Lee, NJ 07024
Manufactured by:
Grifols Therapeutics LLC
Research Triangle Park, NC 27709 USA
U.S. License No. 1871
CONTENTS:
One bottle of Koāte
10 mL Sterile Water for Injection, USP
One sterile Mix2Vial® filter transfer set
No Preservative
For Intravenous Administration Only
Sterile — Nonpyrogenic
Date removed from refrigeration_______________________
GTIN XXXXXXXXXXXXXX
LOT XXXXXXXXXX
EXP DDMMMYYYY
SN XXXXXXXXXXXXXXXX
IU XXXX
NDC 76125-676-50
Koāte®
Antihemophilic
Factor (Human)
Carton: 3046596

NDC 76125-673-51
Koāte®
Antihemophilic Factor (Human)
Solvent/Detergent Treated
Heat-Treated at 80°C
Manufactured for:
Kedrion Biopharma Inc.
400 Kelby Street, Fort Lee, NJ 07024
Manufactured by:
Grifols Therapeutics LLC
Research Triangle Park, NC 27709 USA
U.S. License No. 1871
The patient and physician should discuss the risks and benefits of this product.
No Preservative
For Intravenous Administration Only
Sterile—Nonpyrogenic
Reconstitute with 10 mL Sterile Water for Injection, USP.
Store at 2–8°C (36–46°F) and no more than 6 months at room temperature (up to 25°C; 77°F) at any time prior to the expiration date.
Dosage and Administration: Read package insert.
Rx only
Date removed from refrigeration_____________________
Lot
Exp.
IU
3051812

NDC 13533-000-04 3053017
Nonpyrogenic Single-Dose Container 5 mL
Sterile Water for Injection, USP
for reconstitution of accompanying product
Do not use unless clear. No antimicrobial agent or other
substance has been added. Do not use for intravascular
injection without making approximately isotonic by
addition of suitable solute. Discard unused portion. Rx Only.
Mfd by: Baxter Healthcare Corporation
Deerfield, IL 60015 USA
Mfd for: Grifols Therapeutics LLC
Research Triangle Park, NC 27709 USA
07-32-00-0008
Lot
Exp

NDC 13533-200-05
Sterile Water for Injection, USP 5 mL Rx Only
For reconstitution of accompanying product
Single-Dose Container, Nonpyrogenic
Do not use unless clear. No antimicrobial agent or other
substance has been added. Do not use for intravascular
injection without making approximately isotonic by
addition of suitable solute. Discard unused portion.
Mfd by: Laboratorios Grifols, S. A., Parets del Vallès, Barcelona, 08150 Spain
Mfd for: Grifols Therapeutics LLC, Research Triangle Park, NC, 27709 USA
3051804
Lot / Exp.

NDC 76297-002-02
Sterile Water for Injection, USP
5 mL Rx Only
For reconstitution of accompanying product
Single-Dose Container, Nonpyrogenic
Do not use unless clear. No antimicrobial agent or other substance has been added. Do not use for intravascular injection without making approximately isotonic by addition of suitable solute. Discard unused portion.
Mfd by: Laboratorios Grifols, S.A. Parets del Vallès, Barcelona 08150 Spain
Lot
EXP
3057422